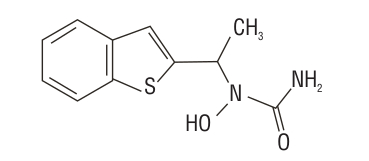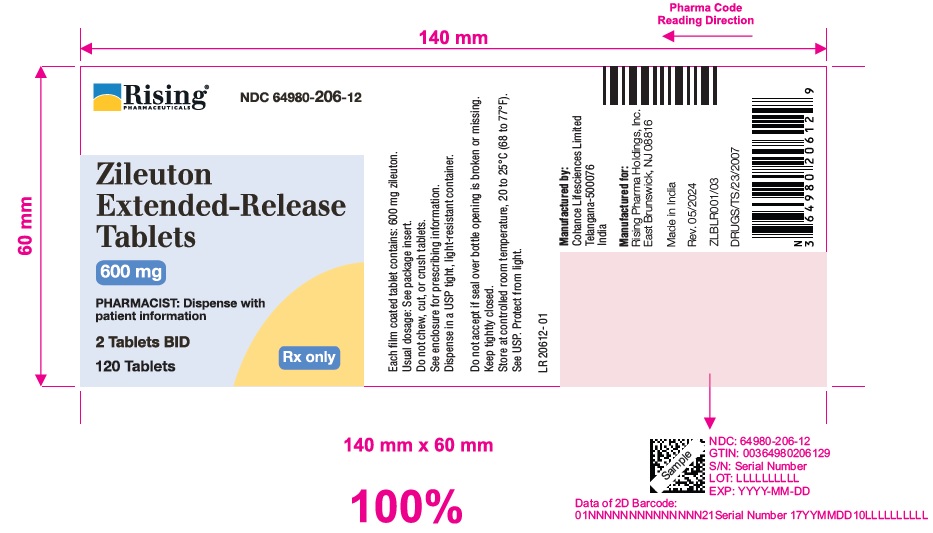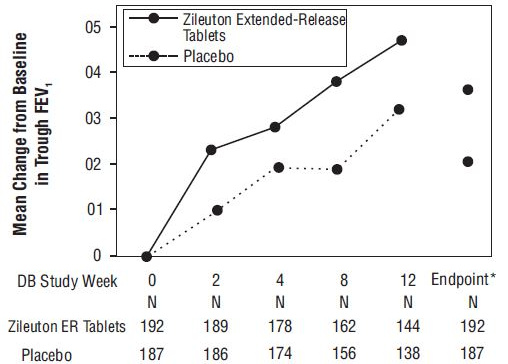 DRUG LABEL: Zileuton
NDC: 64980-206 | Form: TABLET, EXTENDED RELEASE
Manufacturer: Rising Pharma Holdings, Inc.
Category: prescription | Type: Human Prescription Drug Label
Date: 20240515

ACTIVE INGREDIENTS: Zileuton 600 mg/1 1
INACTIVE INGREDIENTS: MANNITOL; MICROCRYSTALLINE CELLULOSE 101; CROSPOVIDONE; STARCH, CORN; SODIUM STARCH GLYCOLATE TYPE A POTATO; SILICON DIOXIDE; SODIUM LAURYL SULFATE; MAGNESIUM STEARATE; FERRIC OXIDE YELLOW; TITANIUM DIOXIDE; POLYETHYLENE GLYCOL 400; HYPROMELLOSE 2208 (200000 MPA.S); HYPROMELLOSE 2208 (15000 MPA.S); HYDROXYPROPYL CELLULOSE (110000 WAMW)

HIGHLIGHTS OF PRESCRIBING INFORMATION

These highlights do not include all the information needed to use ZILEUTON EXTENDED-RELEASE TABLETS safely and effectively. See full prescribing information for ZILEUTON EXTENDED-RELEASE TABLETS.
ZILEUTON extended-release tablets, for oral use
Initial U.S. Approval: 1996

1 INDICATIONS AND USAGE

Zileuton Extended-Release Tablets is a leukotriene synthesis inhibitor indicated for the prophylaxis and chronic treatment of asthma in adults and children 12 years of age and older. (1)

Do not use Zileuton Extended-Release Tablets to treat an acute asthma attack. (1)

2 DOSAGE AND ADMINISTRATION

Adults and children 12 years of age and older: The recommended dose of Zileuton Extended-Release Tablets is two 600 mg extended-release tablets twice daily, within one hour after morning and evening meals, for a total daily dose of 2400 mg. (2)

Monitoring: Assess hepatic function enzymes prior to initiation of Zileuton Extended-Release Tablets and monitor periodically during treatment. (2, 5.1)

3 DOSAGE FORMS AND STRENGTHS

Extended-Release tablets: 600 mg. (3)

4 CONTRAINDICATIONS

- Active liver disease or persistent hepatic function enzyme elevations ≥3 times the upper limit of normal. (4, 5.1)
- History of allergic reaction to Zileuton or any of the ingredients of Zileuton Extended-Release Tablets. (4)

5 WARNINGS AND PRECAUTIONS

Hepatotoxicity: Elevations of one or more hepatic function enzymes and bilirubin may occur with Zileuton Extended-Release Tablets. Assess hepatic function enzymes prior to initiation of Zileuton Extended-Release Tablets, monthly for the first 3 months, every 2-3 months for the remainder of the first year, and periodically thereafter. Use Zileuton Extended-Release Tablets with caution in patients who consume substantial quantities of alcohol and/or have a history of liver disease. (5.1)
Neuropsychiatric Events: Neuropsychiatric events, including sleep disorders and behavior changes, may occur with Zileuton Extended-Release Tablets. Instruct patients to be alert for neuropsychiatric events. Evaluate the risks and benefits of continuing treatment with Zileuton Extended-Release Tablets if such events occur. (5.2)

6 ADVERSE REACTIONS

Most common adverse reactions (≥5%) included: sinusitis, nausea, and pharyngolaryngeal pain. (6.1)

To report SUSPECTED ADVERSE REACTIONS, contact Rising Pharma Holdings, Inc. at 1-844-874-7464 or FDA at 1-800-FDA-1088 or www.fda.gov/medwatch.

7 DRUG INTERACTIONS

- Zileuton increases theophylline levels. Reduce theophylline dose and monitor levels. (7.1)
- Zileuton increases warfarin levels. Monitor prothrombin time and adjust warfarin dose accordingly. (7.2)
- Zileuton increases propranolol levels and beta-blocker activity. Monitor appropriately. (7.3)

8 USE IN SPECIFIC POPULATIONS

Hepatic Impairment: Zileuton Extended-Release Tablets is contraindicated in patients with active liver disease and in patients with elevated hepatic function enzymes ≥3 times the upper limit of normal. (4,5, 8.7)

FULL PRESCRIBING INFORMATION

1 INDICATIONS AND USAGE

Zileuton Extended-Release Tablets is indicated for the prophylaxis and chronic treatment of asthma in adults and children 12 years of age and older.

Zileuton Extended-Release Tablets are not indicated for use in the reversal of bronchospasm in acute asthma attacks. Therapy with Zileuton Extended-Release Tablets can be continued during acute exacerbations of asthma.

2 DOSAGE AND ADMINISTRATION

The recommended dosage of Zileuton Extended-Release Tablets for the treatment of patients with asthma is two 600 mg extended-release tablets twice daily, within one hour after morning and evening meals, for a total daily dose of 2400 mg. Tablets should not be chewed, cut or crushed. If a dose is missed, the patient should take the next dose at the scheduled time and not double the dose. Assess hepatic function enzymes prior to initiation of Zileuton Extended-Release Tablets and periodically during treatment [see Contraindications (4), Warnings and Precautions (5), and Use in Specific Populations (8.7)].

3 DOSAGE FORMS AND STRENGTHS

Extended-release tablets, 600 mg.

4 CONTRAINDICATIONS

The use of Zileuton Extended-Release Tablets is contraindicated in patients with:

- Active liver disease or persistent hepatic function enzyme elevations greater than or equal to 3 times the upper limit of normal (≥3×ULN) [see Warnings and Precautions (5), and Use in Specific Populations (8.7)].
- A history of allergic reaction to zileuton or any of the ingredients of Zileuton Extended Release Tablets (e.g., rash, eosinophilia, etc.).

5 WARNINGS AND PRECAUTIONS

5.1 Hepatotoxicity

Elevations of one or more hepatic function enzymes and bilirubin may occur during Zileuton Extended-Release Tablets therapy. These laboratory abnormalities may progress to clinically significant liver injury, remain unchanged, or resolve with continued treatment, usually within three weeks. The ALT (SGPT) test is considered the most sensitive indicator of liver injury for Zileuton Extended-Release Tablets.

Assess hepatic function enzymes prior to initiation of, and during therapy with, Zileuton Extended-Release Tablets. Assess serum ALT before treatment begins, once a month for the first 3 months, every 2-3 months for the remainder of the first year, and periodically thereafter for patients receiving long-term Zileuton Extended-Release Tablets therapy. If clinical signs and/or symptoms of liver dysfunction develop (e.g., right upper quadrant pain, nausea, fatigue, lethargy, pruritus, jaundice, or “flu-like” symptoms) or transaminase elevations ≥5×ULN occur, discontinue Zileuton Extended-Release Tablets and follow hepatic function enzymes until normal.

In controlled and open-label clinical studies involving more than 5000 patients treated with zileuton immediate-release tablets, the overall rate of ALT elevation ≥3×ULN was 3.2%. In these trials, one patient developed symptomatic hepatitis with jaundice, which resolved upon discontinuation of therapy. An additional 3 patients with transaminase elevations developed mild hyperbilirubinemia that was less than 3×ULN. There was no evidence of hypersensitivity or other alternative etiologies for these findings.

Since treatment with Zileuton Extended-Release Tablets may result in increased hepatic function enzymes and liver injury, Zileuton Extended-Release Tablets should be used with caution in patients who consume substantial quantities of alcohol and/or have a past history of liver disease.

5.2 Neuropsychiatric Events

Neuropsychiatric events have been reported in adult and adolescent patients taking zileuton, the active ingredient in Zileuton Extended-Release Tablets and zileuton immediate-release tablets. Post-marketing reports with zileuton include sleep disorders and behavior changes. The clinical details of some post-marketing reports involving zileuton appear consistent with a drug-induced effect. Patients and prescribers should be alert for neuropsychiatric events. Patients should be instructed to notify their prescriber if these changes occur. Prescribers should carefully evaluate the risks and benefits of continuing treatment with Zileuton Extended-Release Tablets if such events occur [see Adverse Reactions (6.3)].

6 ADVERSE REACTIONS

Hepatotoxicity: Elevations of one or more hepatic function enzymes and bilirubin may occur during Zileuton Extended-Release Tablets therapy [see Warnings and Precautions (5)].

The most commonly occurring adverse reactions (≥5%) with Zileuton Extended-Release Tablets are sinusitis, nausea, and pharyngolaryngeal pain.

6.1 Short-Term Clinical Studies Experience

The safety data described below reflect exposure to Zileuton Extended-Release Tablets in 199 patients for 12 weeks duration. In a 12-week, randomized, double-blind, placebo-controlled trial in adults and adolescents 12 years of age and older with asthma, patients received Zileuton Extended-Release Tablets two 600 mg tablets (n=199) or placebo (n=198) twice daily by mouth. Eighty-three percent of patients were white, 48% were male, and the mean age was 34 years.

Because clinical studies are conducted under widely varying conditions, adverse reaction rates observed in the clinical studies of a drug cannot be directly compared to rates in the clinical studies of another drug and may not reflect the rates observed in practice.

The most commonly reported adverse reactions (occurring at a frequency of ≥5%) in Zileuton Extended-Release Tablets-treated patients and at a frequency greater than placebo-treated patients are reflected in Table 1.

Table 1: Adverse Reactions with ≥5% incidence in a 12-Week Placebo-Controlled Trial in Patients with Asthma.

Adverse Reaction | Zileuton extended- release tablets 2 Tablets Twice Daily N=199 n (%) | Placebo 2 Tablets Twice Daily N = 198 n (%)
Sinusitis | 13 (6.5) | 8 (4.0)
Nausea | 10 (5.0) | 3 (1.5)
Pharyngolaryngeal Pain | 10 (5.0) | 8 (4.0)

Less common adverse reactions occurring at a frequency ≥1% and more often in the Zileuton Extended-Release Tablets group than in the placebo group included gastrointestinal disorders (upper abdominal pain, diarrhea, dyspepsia, vomiting), rash, hypersensitivity, and hepatotoxicity.

There were no differences in the incidence of adverse reactions based upon gender. The clinical trials did not include sufficient numbers of patients <18 years of age or non-Caucasians to determine whether there is any difference in adverse reactions based upon age or race.

Hepatotoxicity

In the 12-week placebo-controlled trial, the incidence of ALT elevations (≥3×ULN) was 2.5% (5 of 199) in the Zileuton Extended-Release Tablets group, compared to 0.5% (1 of 198) in the placebo group. In the Zileuton Extended-Release Tablets group, the majority of ALT elevations (60%) occurred in the first month of treatment, and in 2 of the 5 patients in the Zileuton Extended-Release Tablets group, ALT elevations were detected 14 days after completion of the 3-month study treatment. The levels returned to <2×ULN or normal within 9 and 12 days, respectively. The ALT elevations in the other 3 patients were observed to return to <2×ULN or normal within 15, 19, and 31 days after Zileuton Extended-Release Tablets discontinuation. There appeared to be no clinically relevant relationship between the time of onset and the magnitude of the first elevation or the magnitude of first elevation and time to resolution. The hepatic function enzyme elevations attributed to Zileuton Extended-Release Tablets did not result in any cases of jaundice, development of chronic liver disease, or death in this clinical trial.

6.2 Long-Term Clinical Studies Experience

The safety of Zileuton Extended-Release Tablets was evaluated in one 6-month, randomized, double-blind, placebo-controlled clinical trial in adults and adolescents 12 years of age and older with asthma. Patients received two 600 mg Zileuton Extended-Release Tablets (n=619) or placebo (n=307) twice daily by mouth along with usual asthma care. Eighty-six percent of patients were white, 40% were male, and the overall mean age was 36.

The rate and type of adverse reactions observed in this study were comparable to the adverse reactions observed in the 12-week study. Other commonly reported adverse reactions (occurring at a frequency of ≥5%) in Zileuton Extended-Release Tablets-treated patients and at a frequency greater than placebo-treated patients included the following: headache (23%), upper respiratory tract infection (9%), myalgia (7%), and diarrhea (5%) compared to 21%, 7%, 5% and 2%, respectively, in the placebo-treated group.

ALT elevations (≥3×ULN) were observed in 1.8% of patients treated with Zileuton Extended-Release Tablets compared to 0.7% in patients treated with placebo. The majority of elevations (82%) were reported within the first 3 months of treatment and resolved within 21 days for most of these patients after discontinuation of the drug. The hepatic function enzyme elevations attributed to Zileuton Extended-Release Tablets did not result in any cases of jaundice, development of chronic liver disease, or death in this clinical trial.

Occurrences of low white blood cell (WBC) count (<3.0 × 10^9/L) were observed in 2.6% (15 of 619) of the Zileuton Extended-Release Tablets-treated patients and in 1.7% (5 of 307) of the placebo-treated patients. The WBC counts returned to normal or baseline following discontinuation of Zileuton Extended-Release Tablets. The clinical significance of these findings is not known.

6.3 Post marketing Experience

The following adverse reactions have been identified during post-approval use of zileuton immediate-release tablets and may be applicable to Zileuton Extended-Release Tablets. Because these reactions are reported voluntarily from a population of uncertain size, it is not always possible to reliably estimate their frequency or establish a causal relationship.

Cases of severe hepatic injury have been reported in patients taking zileuton immediate-release tablets. These cases included death, life-threatening liver injury with recovery, symptomatic jaundice, hyperbilirubinemia, and elevations of ALT >8×ULN.

Cases of sleep disorders and behavior changes have also been reported [see Warnings and Precautions (5.2)].

7 DRUG INTERACTIONS

The following study results were obtained using zileuton immediate-release tablets but the conclusions also apply to Zileuton Extended-Release Tablets.

7.1 Theophylline

In a drug-interaction study in 16 healthy subjects, co-administration of multiple doses of zileuton immediate-release tablets (800 mg every 12 hours) and theophylline (200 mg every 6 hours) for 5 days resulted in a significant decrease (approximately 50%) in steady-state clearance of theophylline, an approximate doubling of theophylline AUC, and an increase in theophylline Cmax (by 73%). The elimination half-life of theophylline was increased by 24%. Also, during co-administration, theophylline-related adverse reactions were observed more frequently than after theophylline alone. Upon initiation of Zileuton Extended-Release Tablets in patients receiving theophylline, the theophylline dosage should be reduced by approximately one-half and plasma theophylline concentrations monitored. Similarly, when initiating therapy with theophylline in a patient receiving Zileuton Extended-Release Tablets, the maintenance dose and/or dosing interval of theophylline should be adjusted accordingly and guided by serum theophylline determinations.

7.2 Warfarin

Concomitant administration of multiple doses of zileuton immediate-release tablets (600 mg every 6 hours) and warfarin (fixed daily dose obtained by titration in each subject) to 30 healthy male subjects resulted in a 15% decrease in R-warfarin clearance and an increase in AUC of 22%. The pharmacokinetics of S-warfarin were not affected. These pharmacokinetic changes were accompanied by a clinically significant increase in prothrombin times. Monitoring of prothrombin time, or other suitable coagulation tests, with the appropriate dose titration of warfarin is recommended in patients receiving concomitant Zileuton Extended-Release Tablets and warfarin therapy.

7.3 Propranolol

Co-administration of zileuton immediate-release tablets and propranolol results in a significant increase in propranolol concentrations. Administration of a single 80 mg dose of propranolol in 16 healthy male subjects who received zileuton immediate-release tablets 600 mg every 6 hours for 5 days resulted in a 42% decrease in propranolol clearance. This resulted in an increase in propranolol Cmax, AUC, and elimination half-life by 52%, 104%, and 25%, respectively. There was an increase in β-blockade as shown by a decrease in heart rate associated with the co-administration of these drugs. Patients concomitantly on Zileuton Extended-Release Tablets and propranolol should be closely monitored and the dose of propranolol reduced as necessary. No formal drug-drug interaction studies between zileuton and other beta-adrenergic blocking agents (i.e., β-blockers) have been conducted. It is reasonable to employ appropriate clinical monitoring when these drugs are co-administered with Zileuton Extended-Release Tablets.

7.4 Other Concomitant Drug Therapy

Drug-drug interaction studies conducted in healthy subjects between zileuton immediate-release tablets and prednisone and ethinyl estradiol (oral contraceptive), drugs known to be metabolized by the CYP3A4 isoenzyme, have shown no significant interaction. However, no formal drug-drug interaction studies between zileuton and CYP3A4 inhibitors, such as ketaconazole, have been conducted. It is reasonable to employ appropriate clinical monitoring when these drugs are co-administered with Zileuton Extended-Release Tablets. Drug-drug interaction studies in healthy subjects have been conducted with zileuton immediate-release tablets and digoxin, phenytoin, sulfasalazine, and naproxen. There was no significant interaction between zileuton and any of these drugs.

8 USE IN SPECIFIC POPULATIONS

Information on specific populations is based on studies conducted with zileuton immediate-release tablets and is applicable to Zileuton Extended-Release Tablets.

8.1 Pregnancy

Risk Summary:

There are no adequate human data on zileuton use in pregnant women to inform a drug associated risk. In animal studies, oral administration of zileuton to pregnant rats and rabbits during organogenesis produced adverse developmental outcomes. Structural abnormalities (cleft palate) were observed in rabbits at a dose similar to the maximum recommended human daily oral dose (MRHD), and alterations to growth (reduced fetal body weight and increased skeletal variations) were observed in rats at maternal plasma exposures 20 times greater than at the MRHD [see Data]. In a pre- and post-natal development study, oral administration of zileuton to pregnant rats from organogenesis through weaning at maternal plasma exposures 20 times greater than the MRHD resulted in reduced pup survival and body weights. Zileuton and/or its metabolites cross the placental barrier of rats; therefore, zileuton may be transmitted from the mother to the developing fetus.
In the U.S. general population, the estimated background risk of major birth defects and miscarriage in clinically recognized pregnancies is 2-4% and 15-20%, respectively.

Pregnancy Exposure Registry:

There is a pregnancy exposure registry that monitors pregnancy outcomes in women exposed to asthma medications during pregnancy. For more information, contact the MothersToBaby Pregnancy Studies conducted by the Organization of Teratology Information Specialists at 1-877-311-8972 or visit http://mothertobaby.org/pregnancy-studies/.

Data

Animal Data

In a fertility and general reproductive performance study in rats, 0, 15, 75, 150 or 300 mg/kg/day zileuton was administered orally to male and female rats. The treated males were dosed daily for 100 days prior to mating with the treated females and 80 days prior to mating with untreated females, and throughout the mating periods. The treated females were dosed for 14 days before mating with untreated males and dosing continued throughout gestation, and in 1/3 of the females through parturition and lactation period. Maternal body weight gain was reduced at 150 and 300 mg/kg/day groups (9-12% differences in body weight relative to controls).

During fetal evaluation, zileuton produced lower litter size (7.1 pup/dams at 300 mg/kg/day vs. 9.6 pup/dams at 150 mg/kg/day vs. 13.5 pup/dams in control group), lower fetal weights (-9%), decreased viable fetuses, and increased in unossification of fetal skeletal structure at 300 mg/kg at exposures greater than 20 times the MRHD (on an AUC basis with data obtained from the comparable doses of 3-month general toxicity study). There were no embryofetal effects at 150 mg/kg/day.

During post-natal development evaluation, zileuton produced decrease in pup viability (-16% at 150 mg/kg/day and -43.5% at 300 mg/kg/day on lactation Day 4) as well as depression of body weight gain in pups at ≥ 150 mg/kg/day at exposures close to 20 times the MRHD (on an AUC basis with data obtained from the comparable doses of 1-year general toxicity study). Observations of lower pup weight and survival rate at 300 mg/kg/day group were confirmed in a peri- & post-natal study administered with the same dose levels in pregnant rats.

In a teratology study in pregnant rabbits, 0, 15, 50 or 150 mg/kg/day zileuton was administered orally to pregnant animals during organogenesis. Cleft palate was noted in three of 118 (2.5%) rabbit fetuses (or 2 of 17 litters) at 150 mg/kg/day. Additionally, two fetuses (1.7%) had domed head and two fetuses (1.7%) had hydrocephalus also at 150 mg/kg/day which was equivalent to the MRHD on a mg/m^2 basis. There were no adverse developmental outcomes at 50 mg/kg/day (approximately one-third the MRHD on a mg/m^2 basis).

Oral dose of 5 mg radiolabeled zileuton indicated that zileuton crosses the placental barrier of rats.

8.2 Lactation

Risk Summary

Zileuton and/or its metabolites are excreted in rat milk. It is not known if zileuton is excreted in human milk, nor are there data on the effects of the drug on the breastfed infant or effects on maternal milk production. Because many drugs are excreted in human milk, and because of the potential for tumorigenicity of zileuton shown in animal studies, the developmental and health benefits of breastfeeding should be considered along with the mother's clinical need for zileuton and any potential adverse effects on the breastfed child from zileuton or from the underlying maternal condition.

Data

Animal Data

Following an oral 70 mg/kg dose of radiolabeled ^14C-zileuton to lactating rats, total radioactivity was distributed into the milk of dams, but the mean concentrations did not exceed those in plasma.

8.4 Pediatric Use

The safety and effectiveness of Zileuton Extended-Release Tablets in pediatric patients under 12 years of age have not been established. FDA has not required pediatric studies in patients under the age of 12 years due to the risk of hepatotoxicity. Zileuton Extended-Release Tablets is not appropriate for children less than 12 years of age.

8.5 Geriatric Use

Subgroup analysis of controlled and open-label clinical studies with zileuton immediate-release tablets suggests that females ≥65 years of age appear to be at increased risk of ALT elevations. In Zileuton Extended-Release Tablets placebo-controlled studies there were no discernable trends in ALT elevations noted in subset analyses for patients ≥65 years of age, although the database may not have been sufficiently large to detect a trend [see Pharmacokinetics (12.3)].

8.6 Renal Impairment

Dosing adjustment in patients with renal dysfunction or patients undergoing hemodialysis is not necessary [see Pharmacokinetics (12.3)].

8.7 Hepatic Impairment

Zileuton Extended-Release Tablets is contraindicated in patients with active liver disease or persistent ALT elevations ≥3×ULN [see Warnings and Precautions (5) and Pharmacokinetics (12.3)].

10 OVERDOSAGE

Human experience of acute overdose with zileuton is limited. A patient in a clinical study took between 6.6 and 9.0 grams of zileuton immediate-release tablets in a single dose. Vomiting was induced and the patient recovered without sequelae. Zileuton is not removed by dialysis. Should an overdose occur, the patient should be treated symptomatically and supportive measures instituted as required. If indicated, elimination of unabsorbed drug should be achieved by emesis or gastric lavage; usual precautions should be observed to maintain the airway. A Certified Poison Control Center should be consulted for up-todate information on management of overdose with Zileuton Extended-Release Tablets.

The oral minimum lethal doses in mice and rats were 500-4000 and 300-1000 mg/kg, respectively (providing greater than 3 and 9 times the systemic exposure [AUC] achieved at the maximum recommended human daily oral dose, respectively). In dogs, at an oral dose of 1000 mg/kg (providing in excess of 12 times the systemic exposure [AUC] achieved at the maximum recommended human daily oral dose) no deaths occurred but nephritis was reported.

11 DESCRIPTION

Zileuton is an orally active inhibitor of 5-lipoxygenase, the enzyme that catalyzes the formation of leukotrienes from arachidonic acid. Zileuton has the chemical name (±)-1-(1-Benzo[b]thien-2-ylethyl)-1-hydroxyurea and the following chemical structure:

Zileuton has the molecular formula C11H12N2O2S and a molecular weight of 236.29. It is a racemic mixture (50:50) of R(+) and S(-) enantiomers. Zileuton is a practically odorless, white, crystalline powder that is soluble in methanol and ethanol, slightly soluble in acetonitrile, and practically insoluble in water and hexane. The melting point ranges from 144.2°C to 145.2°C.

Zileuton Extended-Release Tablets for oral administration are bi-layer tablets comprising of an immediate-release layer and extended-release layer. Zileuton Extended-Release Tablets are oval shaped, biconvex tablets debossed with “656” on one side and “P” on the other side. Each tablet contains 600 mg of zileuton and the following inactive ingredients: colloidal silicon dioxide, crospovidone, hydroxypropyl cellulose, hypromellose, magnesium stearate, mannitol, microcrystalline cellulose, partially pregelatinized maize starch, polyethylene glycol 400, sodium lauryl sulfate, sodium starch glycolate, titanium dioxide, yellow iron oxide.

12 CLINICAL PHARMACOLOGY

12.1 Mechanism of Action

Zileuton is an inhibitor of 5-lipoxygenase and thus inhibits leukotriene (LTB4, LTC4, LTD4 and LTE4) formation. Both the R(+) and S(-) enantiomers are pharmacologically active as 5-lipoxygenase inhibitors in in vitro and in vivo systems. Leukotrienes are substances that induce numerous biological effects including augmentation of neutrophil and eosinophil migration, neutrophil and monocyte aggregation, leukocyte adhesion, increased capillary permeability, and smooth muscle contraction. These effects contribute to inflammation, edema, mucus secretion, and bronchoconstriction in the airways of asthmatic patients. LTB4, a chemoattractant for neutrophils and eosinophils, and cysteinyl leukotrienes (LTC4, LTD4, LTE4) can be measured in a number of biological fluids including bronchoalveolar lavage fluid (BALF), blood, urine and sputum from asthmatic patients.

Zileuton is an orally active inhibitor of ex vivo LTB4 formation in several species, including mice, rats, rabbits, dogs, sheep, and monkeys. Zileuton inhibits arachidonic acid-induced ear edema in mice, neutrophil migration in mice in response to polyacrylamide gel, and eosinophil migration into the lungs of antigen-challenged sheep. In a mouse model of allergic inflammation, zileuton inhibited neutrophil and eosinophil influx, reduced the levels of multiple cytokines in the BALF, and reduced serum IgE levels. Zileuton inhibits leukotriene-dependent smooth muscle contractions in vitro in guinea pig and human airways. The compound inhibits leukotriene-dependent bronchospasm in antigen and arachidonic acid-challenged guinea pigs. In antigen-challenged sheep, zileuton inhibits late-phase bronchoconstriction and airway hyperreactivity. The clinical relevance of these findings is unknown.

12.2 Pharmacodynamics

Zileuton is an orally active inhibitor of ex vivo LTB4 formation in humans. The inhibition of LTB4 formation in whole blood is directly related to zileuton plasma levels. In patients with asthma, the IC50 is estimated to be 0.46 μg/mL, and maximum inhibition ≥80% is reached at a zileuton concentration of 2 μg/mL. In patients with asthma receiving zileuton immediate-release tablets 600 mg four times daily, peak plasma levels averaging 5.9 μg/mL were associated with a mean LTB4 inhibition of 98%. Zileuton inhibits the synthesis of cysteinyl leukotrienes as demonstrated by reduced urinary LTE4 levels.

12.3 Pharmacokinetics

Information on the pharmacokinetics of zileuton following the administration of zileuton immediate-release tablets is available in healthy subjects. The results of two clinical pharmacology studies using Zileuton Extended-Release Tablets are described below.

Absorption

A three-way crossover study was conducted in healthy male and female subjects (n=23) with a mean age of 33 (range 20-55) following single dose of 1200 mg (2 × 600 mg) Zileuton Extended-Release Tablets under fasted and fed conditions, and two doses of 600 mg zileuton immediate-release tablets every 6 hours under fasted conditions. Food increased the peak mean plasma concentrations (Cmax) and the mean extent of absorption (AUC) of Zileuton Extended-Release Tablets by 18 and 34%, respectively, and prolonged Tmax from 2.1 hours to 4.3 hours. The relative bioavailability of Zileuton Extended-Release Tablets to zileuton immediate-release tablets with respect to Cmax and AUC under fasted conditions were 0.39 (90% CI: 0.36, 0.43) and 0.57 (90% CI: 0.52, 0.62), respectively. Similarly, relative bioavailability of Zileuton Extended-Release Tablets to zileuton immediate-release tablets with respect to Cmax and AUC under fed conditions were 0.45 (90% CI: 0.41, 0.49) and 0.76 (90% CI: 0.70, 0.83), respectively.

A three-way crossover study was conducted in healthy male and female subjects (n=24) with a mean age of 35 (range 19-56) following multiple doses of 1200 mg (2 × 600 mg) Zileuton Extended-Release Tablets administered every 12 hours under fasted and fed conditions, and 600 mg zileuton immediate-release tablets every 6 hours under fed conditions until steady state zileuton levels were achieved. Food increased AUC and Cmin of Zileuton Extended-Release Tablets by 43% and 170%, respectively, but had no effect on Cmax. Therefore, Zileuton Extended-Release Tablets is recommended to be administered with food [see Dosage and Administration (2)]. At steady state, relative bioavailability of Zileuton Extended-Release Tablets to zileuton immediate-release tablets with respect to Cmax, Cmin, and AUC were 0.65 (90% CI: 0.60, 0.71), 1.05 (90% CI: 0.88, 1.25) and 0.85 (90% CI: 0.78, 0.92) respectively. These data indicate that at steady state under fed conditions the Cmax of Zileuton Extended-Release Tablets is about 35% lower than that of zileuton immediate-release tablets but the Cminand AUC are similar for both formulations.

Distribution

The apparent volume of distribution (V/F) of zileuton is approximately 1.2 L/kg. Zileuton is 93% bound to plasma proteins, primarily to albumin, with minor binding to α1–acid glycoprotein.

Elimination

Elimination of zileuton is predominantly via metabolism with a mean terminal half-life of 3.2 hours. Apparent oral clearance (CL/F) of zileuton is 669 mL/min. Zileuton activity is primarily due to the parent drug. Studies with radiolabeled drug have demonstrated that orally administered zileuton is well absorbed into the systemic circulation with 94.5% and 2.2% of the radiolabeled dose recovered in urine and feces, respectively.

Metabolism

In vitro studies utilizing human liver microsomes have shown that zileuton and its N-dehydroxylated metabolite can be oxidatively metabolized by CYP1A2, CYP2C9 and CYP3A4.

Several zileuton metabolites have been identified in human plasma and urine. These include two diastereomeric O-glucuronide conjugates (major metabolites) and an N-dehydroxylated metabolite (A-66193) of zileuton. The urinary excretion of the inactive A-66193 metabolite and unchanged zileuton each accounted for less than 0.5% of the single radiolabeled dose. Multiple doses of 1200 mg Zileuton Extended-Release Tablets twice daily resulted in peak plasma levels of 4.9 μg/mL of the inactive metabolite A-66193 with an AUC of 93 μg hr/mL, showing large inter-subject variability. This inactive metabolite has been shown to be formed by the gastrointestinal microflora prior to the absorption of zileuton and its formation increases with delayed absorption of zileuton.

Renal Impairment

The pharmacokinetics of zileuton immediate-release tablets were similar in healthy subjects and in subjects with mild, moderate, and severe renal insufficiency. In subjects with renal failure requiring hemodialysis, zileuton pharmacokinetics were not altered by hemodialysis and a very small percentage of the administered zileuton dose (<0.5%) was removed by hemodialysis. Hence, dosing adjustment in patients with renal dysfunction or undergoing hemodialysis is not necessary.

Hepatic Impairment

The pharmacokinetics of zileuton immediate-release tablets were compared between subjects with mild and moderate chronic hepatic insufficiency. The mean apparent plasma clearance of total zileuton in subjects with hepatic impairment was approximately half the value of the healthy subjects. The percent binding of zileuton to plasma proteins after multiple dosing was significantly reduced in patients with moderate hepatic impairment. Zileuton Extended-Release Tablets is contraindicated in patients with active liver disease or persistent ALT elevations ≥3×ULN [see Warnings and Precautions (5)].

Geriatric Use

The pharmacokinetics of zileuton immediate-release tablets were investigated in healthy elderly subjects (ages 65 to 81 years, 9 males, 9 females) and healthy young subjects (ages 20 to 40 years, 5 males, 4 females) after single and multiple oral doses of 600 mg zileuton every 6 hours. Zileuton pharmacokinetics were similar in healthy elderly subjects (≥65 years) compared to healthy younger adults (20 to 40 years).

13 NONCLINICAL TOXICOLOGY

13.1 Carcinogenesis, Mutagenesis, Impairment of Fertility

In 2-year carcinogenicity studies, increases in the incidence of liver, kidney, and vascular tumors in female mice and a trend toward an increase in the incidence of liver tumors in male mice were observed at 450 mg/kg/day (providing approximately 5 times [females] or 8 times [males] the systemic exposure [AUC=64 μg hr/mL] achieved at the maximum recommended human daily oral dose).

No increase in the incidence of tumors was observed at 150 mg/kg/day (providing approximately 2-3 times the systemic exposure [AUC] achieved at the maximum recommended human daily oral dose). In rats, an increase in the incidence of kidney tumors was observed in both sexes at 170 mg/kg/day (providing approximately 8 times [males] or 16 times [females] the systemic exposure [AUC] achieved at the maximum recommended human daily oral dose). No increased incidence of kidney tumors was seen at 80 mg/kg/day (providing approximately 4 times [males] or 7 times [females] the systemic exposure [AUC] achieved at the maximum recommended human daily oral dose). Although a dose-related increased incidence of benign Leydig cell tumors was observed, Leydig cell tumorigenesis was prevented by supplementing male rats with testosterone.

Zileuton was negative in genotoxicity studies including bacterial reverse mutation (Ames) using S. typhimurium and E. coli, chromosome aberration in human lymphocytes, in vitro unscheduled DNA synthesis (UDS), in rat hepatocytes with or without zileuton pretreatment and in mouse and rat kidney cells with zileuton pretreatment, and mouse micronucleus assays. However, a dose-related increase in DNA adduct formation was reported in kidneys and livers of female mice treated with zileuton. Although some evidence of DNA damage was observed in a UDS assay in hepatocytes isolated from Aroclor-1254-treated rats, no such finding was noticed in hepatocytes isolated from monkeys, where the metabolic profile of zileuton is more similar to that of humans.

In reproductive performance/fertility studies, zileuton produced no effects on fertility in rats at oral doses up to 300 mg/kg/day (providing approximately 12 times [male rats] and greater than 10 times [female rats] the systemic exposure [AUC] achieved at the maximum recommended human daily oral dose). Comparative systemic exposure (AUC) is based on measurements in male rats or nonpregnant female rats at similar dosages. However, reduction in fetal implants was observed at oral doses of 150 mg/kg/day and higher (providing approximately 10 times the systemic exposure [AUC] achieved at the maximum recommended human daily oral dose). These effects were not seen at an estimated 4 times clinical exposure. Increases in gestation length, prolongation of estrus cycle, and increases in stillbirths were observed at oral doses of 70 mg/kg/day and higher (providing approximately 3 times the systemic exposure [AUC] achieved at the maximum recommended human daily oral dose). In a perinatal/postnatal study in rats, reduced pup survival and growth were noted at an oral dose of 300 mg/kg/day (providing approximately greater than 10 times the systemic exposure [AUC] achieved at the maximum recommended human daily oral dose).

14 CLINICAL STUDIES

The efficacy of Zileuton Extended-Release Tablets was evaluated in a randomized, double-blind, parallel-group, placebo-controlled, multicenter trial of 12 weeks duration in patients 12 years of age and older with asthma. The 12-week trial included 199 patients randomized to Zileuton Extended-Release Tablets (two 600 mg tablets twice daily) and 198 to placebo. Eighty-three percent of patients were white, 48% were male, and the mean age was 34 years. The mean baseline FEV1 percent predicted was 58.5%.

Assessment of efficacy was based upon forced expiratory volume in one second (FEV1) at 12 weeks. Zileuton Extended-Release Tablets demonstrated a significantly greater improvement in mean change from baseline trough FEV1 at 12 weeks compared to placebo (0.39 L vs. 0.27 L; p=0.021). The mean change from baseline FEV1 over the course of the 12-week study is shown in Figure 1. Secondary endpoints (PEFR and rescue beta-agonist use) were supportive of efficacy.

Examination of gender subgroups did not identify differences in response between men and women. The database was not large enough to assess whether there were differences in response in age or racial subgroups.

Figure 1. Mean Change from Baseline in Trough FEV1 in 12-Week Clinical Trial in Patients with Asthma.

Mean Change from Baseline in Trough Forced
Expiratory Volume After 1 Second in 12-Week Clinical Trial in Patients With Asthma.

*p ≤0.050. Endpoint analysis based on last-observation-carried-forward (LOCF) methodology

16 HOW SUPPLIED/STORAGE AND HANDLING

Zileuton Extended-Release Tablets are yellow colored, oval shaped, biconvex tablets debossed with “656” on one side and “P” on the other side; they are supplied in bottles of 120 tablets (NDC 64980-206-12).

Store between 20 to 25°C (68 to 77°F); excursions permitted to 15-30°C (59 to 86°F) [see USP Controlled Room Temperature]. Protect from light.

17 PATIENT COUNSELING INFORMATION

17.1 Information for Patients

Patients should be told that:

- Zileuton Extended-Release Tablets is indicated for the chronic treatment of asthma and should be taken regularly as prescribed, even during symptom-free periods.
- Zileuton Extended-Release Tablets is a leukotriene synthesis inhibitor which works by inhibiting the formation of leukotrienes.
- Zileuton Extended-Release Tablets should be taken within one hour after morning and evening meals.
- Zileuton Extended-Release Tablets should not be cut, chewed or crushed.
- Zileuton Extended-Release Tablets is not a bronchodilator and should not be used to treat acute episodes of asthma.
- When taking Zileuton Extended-Release Tablets, they should not decrease the dose or stop taking any other antiasthma medications unless instructed by a health care provider. If a dose is missed, they should take the next dose at the scheduled time and not double the dose.
- While using Zileuton Extended-Release Tablets, medical attention should be sought if short-acting bronchodilators are needed more often than usual, or if more than the maximum number of inhalations of short-acting bronchodilator treatment prescribed for a 24-hour period are needed.
- The most serious side effect of Zileuton Extended-Release Tablets is potential elevation of liver enzymes (in 2% of patients) and that, while taking Zileuton Extended-Release Tablets, they must return for liver enzyme test monitoring on a regular basis.
- If they experience signs and/or symptoms of liver dysfunction (e.g., right upper quadrant pain, nausea, fatigue, lethargy, pruritus, jaundice, or “flu-like” symptoms), they should contact their health care provider immediately.
- Patients should be instructed to notify their healthcare provider if neuropsychiatric events occur while using Zileuton Extended-Release Tablets.
- Zileuton Extended-Release Tablets can interact with other drugs and that, while taking Zileuton Extended-Release Tablets, they should consult their health care provider before starting or stopping any prescription or non-prescription medicines.
- A patient leaflet is included with the tablets.

Manufactured by:
Cohance Lifesciences Limited
Telangana 500076, India

Manufactured for:
Rising Pharma Holdings, Inc.
East Brunswick, NJ 08816

Made in India
DRUGS/TS/23/2007
PIR20612-01

Revised: 05/2024

PATIENT INSTRUCTIONS LEAFLET (PIL)

17.2 FDA-Approved Patient Labeling

Zileuton Extended-Release Tablets
Read the Patient Information that comes with Zileuton Extended-Release Tablets carefully before you start taking it and read it each time you get a refill. There may be new information. This leaflet does not take the place of talking with your health care provider about your medical condition or your treatment.

What is Zileuton Extended-Release Tablets?
Zileuton Extended-Release Tablets is a medicine that is used to prevent asthma attacks and for long-term management of asthma in adults and children 12 years of age and older. Zileuton Extended-Release Tablets blocks the production of leukotrienes. Leukotrienes are substances that may contribute to your asthma.

Zileuton Extended-Release Tablets is not a rescue medicine (it is not a bronchodilator) and should not be used if you need relief right away for an asthma attack.

Who should not take Zileuton Extended-Release Tablets?
Do not take Zileuton Extended-Release Tablets if you have:

- active liver disease or repeated blood tests showing elevated liver enzymes (substances released by the liver).
- ever had an allergic reaction to Zileuton Extended-Release Tablets or any of the ingredients in Zileuton Extended-Release Tablets.

What should I tell my health care provider before taking Zileuton Extended-Release Tablets?
Zileuton Extended-Release Tablets may not be right for you. Tell your health care provider if you:

- have ever had liver problems, including hepatitis, jaundice (yellow eyes or skin), or dark urine.
- drink alcohol. Tell your health care provider how much and how often you drink alcohol.
- have difficulty swallowing pills.
- are pregnant or planning to become pregnant. It is not known if Zileuton Extended-Release Tablets will harm your unborn baby. Do not take Zileuton Extended-Release Tablets during pregnancy unless you and your health care provider decide that taking the medicine is more important than the possible risk to your unborn baby.
- are breastfeeding. It is not known if Zileuton Extended-Release Tablets passes into your breast milk. You and your health care provider should decide if you will take Zileuton Extended-Release Tablets or breastfeed. You should not do both.

Tell your health care provider about all the medicines you take, including prescription and non-prescription medicines, vitamins, and herbal supplements. Zileuton Extended-Release Tablets and other medications may affect each other causing side effects. Your health care provider may need to adjust the dose of certain medicines while you are taking Zileuton Extended-Release Tablets. Talk with your health care provider before starting or stopping any prescription or nonprescription medicine.

Know the medicines you take. Keep a list of your medicines and show it to your health care provider and pharmacist when you get a new medicine.

How should I take Zileuton Extended-Release Tablets?

- Take Zileuton Extended-Release Tablets exactly as prescribed by your health care provider. Do not decrease the dose of Zileuton Extended-Release Tablets or stop taking the medicine without talking to your health care provider first, even if you have no asthma symptoms.
- Take two Zileuton Extended-Release Tablets two times each day within one hour after your morning and evening meals.
- Swallow Zileuton Extended-Release Tablets whole. Do not chew, cut or crush Zileuton Extended-Release Tablets. Tell your health care provider if you cannot swallow the tablets whole.
- Follow your health care provider’s instructions for what to do if you get sudden symptoms of an asthma attack. You can continue taking Zileuton Extended-Release Tablets during asthma attacks.
- Get medical help right away if you need to use your rescue medicine more often than usual or if you use the highest number of “puffs” prescribed for one 24 hour period. These could be signs that your asthma is getting worse. This means that your asthma therapy may need to be changed.
- Keep taking your other asthma medicines as directed while taking Zileuton Extended-Release Tablets.
- If you miss a dose, just take your next scheduled dose when it is due. Do not double the dose.
- If you take too much Zileuton Extended-Release Tablets, call your health care provider or a Poison Control Center right away.

What are the possible side effects of Zileuton Extended-Release Tablets?
Zileuton Extended-Release Tablets can cause serious side effects.

Liver problems. Liver function enzymes and bilirubin can increase while taking Zileuton Extended-Release Tablets, and severe liver injury can occur.

Sleep disorders and changes in your behavior can happen while you take Zileuton Extended-Release Tablets. Tell your healthcare provider if you have any sleep problems or changes in behavior.

- Keep all of your health care provider's appointments and be sure to follow all of your health care provider's instructions. Have your blood tests done as ordered to check your liver enzymes.
- Tell your health care provider right away if you get any of the following signs or symptoms: pain on the right side of your abdomen (stomach area), nausea, tiredness, lack of energy, itching, yellow skin or yellow color in the whites of your eyes, dark urine, or “flu-like” symptoms.

Some of the most common side effects are:

- nose and throat irritation
- sinusitis
- upper respiratory infection
- throat pain
- headache
- muscle aches
- nausea
- diarrhea

Allergic reactions can happen while taking Zileuton Extended-Release Tablets. Tell your health care provider right away if you get any of the following signs or symptoms: rash or hives.

Tell your health care provider if you have any new or unusual symptoms that bother you or do not go away while taking Zileuton Extended-Release Tablets.

These are not all of the possible side effects of Zileuton Extended-Release Tablets. For more information, ask your health care provider or pharmacist.

How should I store Zileuton Extended-Release Tablets?

- Store at controlled room temperature, 20 to 25°C (68° to 77°F) see USP. Protect from light.
- Protect Zileuton Extended-Release Tablets from light and replace the cap each time after use.

Keep Zileuton Extended-Release Tablets and all medicines out of the reach of children.

General Information about Zileuton Extended-Release Tablets:

Medicines are sometimes prescribed for conditions that are not mentioned in the patient leaflet. Do not use Zileuton Extended-Release Tablets for a condition for which it was not prescribed. Do not give Zileuton Extended-Release Tablets to other people, even if they have the same symptoms you have. It may harm them.

This patient information leaflet summarizes the most important information about Zileuton Extended-Release Tablets. If you would like more information about Zileuton Extended-Release Tablets, talk with your health care provider or pharmacist. You can ask your health care provider or pharmacist for information about Zileuton Extended-Release Tablets that is written for health professionals.

For more information contact
Rising Pharma Holdings, Inc. at 1-844-874-7464

What are the ingredients in Zileuton Extended-Release Tablets?
Active ingredient: zileuton

Inactive ingredients: colloidal silicon dioxide, crospovidone, hydroxypropyl cellulose, hypromellose, magnesium stearate, mannitol, microcrystalline cellulose, partially pregelatinized maize starch, polyethylene glycol 400, sodium lauryl sulfate, sodium starch glycolate, titanium dioxide, yellow iron oxide.

Manufactured By:
Cohance Lifesciences Limited
Telangana 500076, India

Manufactured for:
Rising Pharma Holdings, Inc.
East Brunswick, NJ 08816
Made in India
DRUGS/TS/23/2007
Revised: 05/2024
PILR20612-01

PACKAGE LABEL

———PRINCIPAL DISPLAY PANEL———

Rising® NDC 64980-206-12
Zileuton
Extended-Release
Tablets
600 mg
PHARMACIST: Dispense with
patient information
2 Tablets BID
120 Tablets Rx only